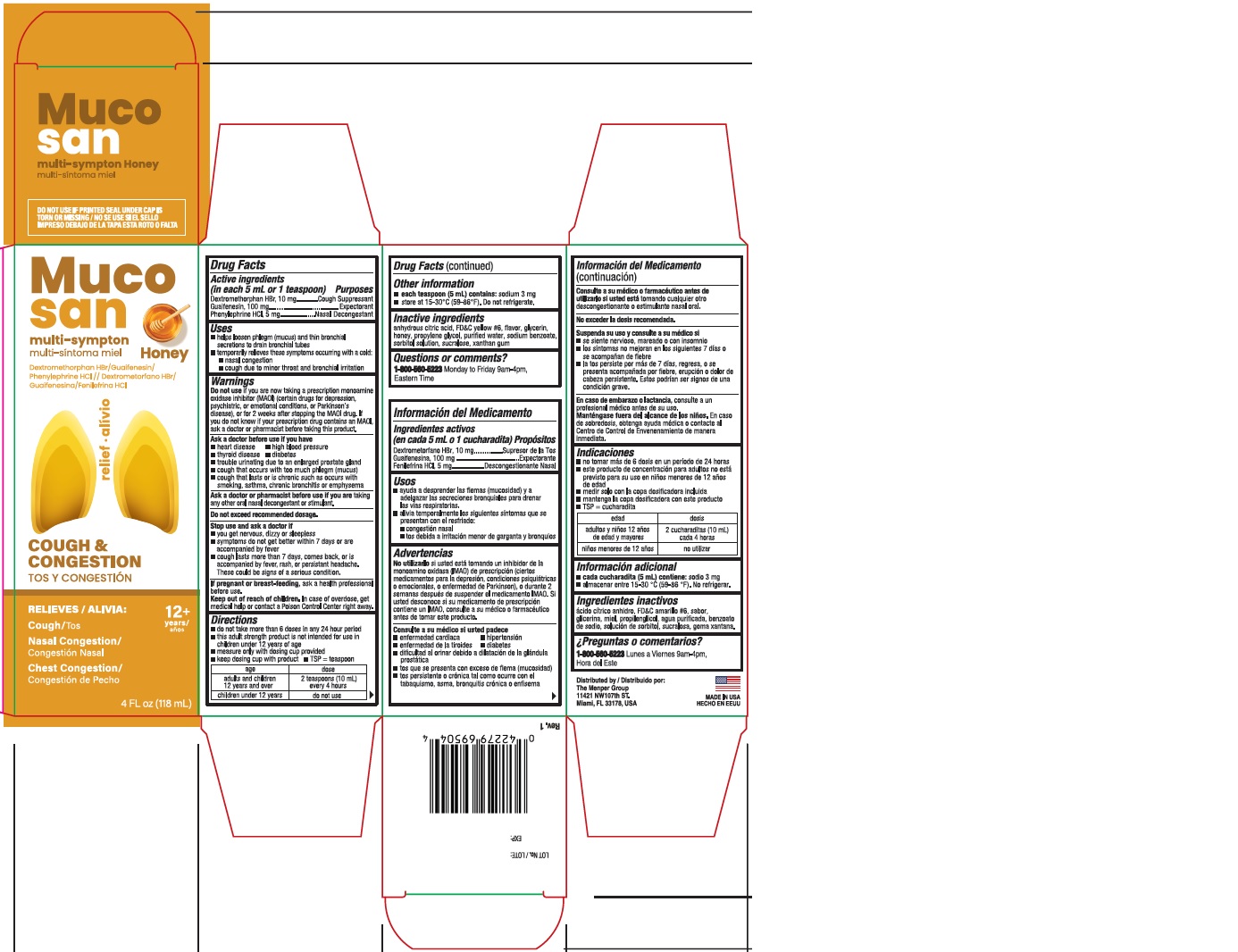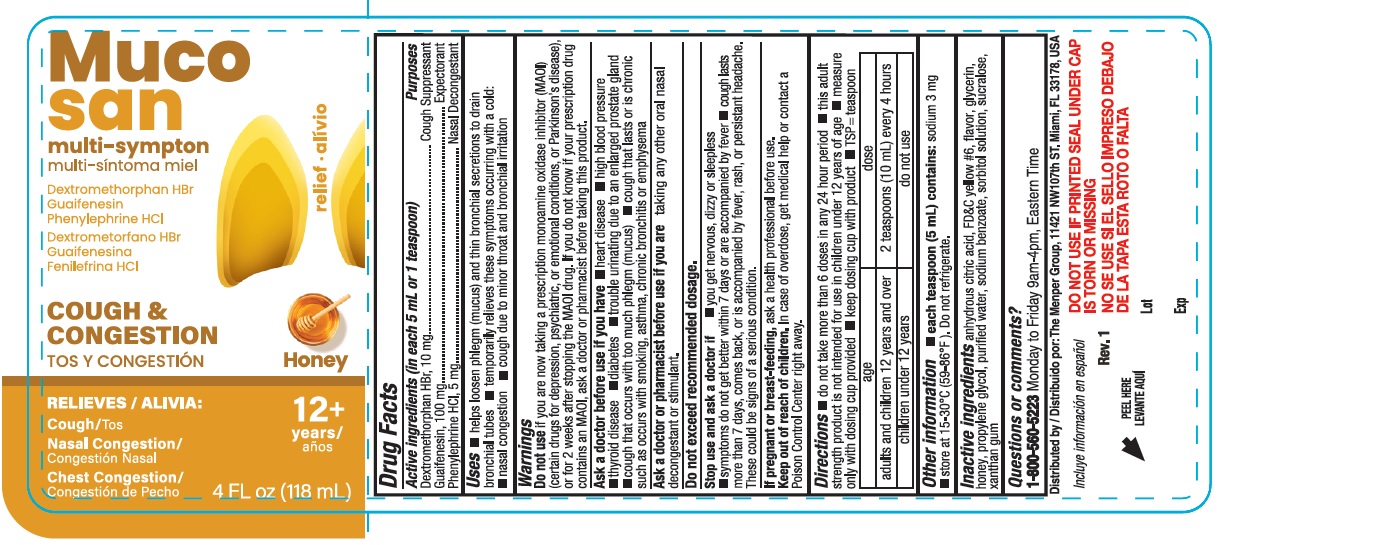 DRUG LABEL: Mucosan Multi-Symptom Honey
NDC: 53145-695 | Form: LIQUID
Manufacturer: Menper Distributors, Inc.
Category: otc | Type: HUMAN OTC DRUG LABEL
Date: 20260108

ACTIVE INGREDIENTS: DEXTROMETHORPHAN HYDROBROMIDE 10 mg/5 mL; GUAIFENESIN 100 mg/5 mL; PHENYLEPHRINE HYDROCHLORIDE 5 mg/5 mL
INACTIVE INGREDIENTS: ANHYDROUS CITRIC ACID; FD&C YELLOW NO. 6; SUCRALOSE; SODIUM BENZOATE; HONEY; WATER; XANTHAN GUM; GLYCERIN; PROPYLENE GLYCOL; SORBITOL SOLUTION

Mucosan Multi-Symptom Honey

ACTIVE INGREDIENT

Active ingredients (in each 5 mL or 1 teaspoon) Purposes

Dextromethorphan HBr, 10 mg............................Cough suppressant
Guaifenesin, 100 mg...........................................Expectorant
Phenylephrine HCl, 5 mg....................................Nasal decongestant

Purposes

Cough suppressant
Expectorant
Nasal decongestant

Uses

- helps loosen phlegm (mucus) and thin bronchial secretions to drain bronchial tubes
- temporarily relieves these symptoms occurring with a cold:
- nasal congestion
- cough due to minor throat and bronchial irritation

WARNINGS

Do not useif you are now taking a prescription monoamine oxidase inhibitor (MAOI) (certain drugs for depression, psychiatrixm or emotional conditions, or Parkinson's disease), or for 2 weeks after stopping the MAOI drug. If you do not know if your prescroption drug contains an MAOI, ask a doctor or pharmacist before taking this product.

Ask a doctor before use if you have

- heart disease
- high blood pressure
- thyroid disease
- diabetes
- trouble urinating due to an enlarged prostate gland
- cough that occurs with too much phlegm (musus)
- cough that lasts or is chronic such as occurs with smoking, asthma, chronic bronchitis or emphysema

Ask a doctor or pharmacist before use if you aretaking any other oral nasal decongestant or stimulant.

OVERDOSAGE

Do not exceed recommended dosage.

Stop use and ask a doctor if

- you get nervous, dizzy or sleepless
- symptoms do not get better within 7 days or are accompanied by fever
- cough lasts more than 7 days, comes back, or is accompanied by fever, rash, or persistant headache. These could be signs of a serious condition.

PREGNANCY OR BREAST FEEDING

If pregnant or breast - feeding,ask a health proffessional before use.

Keep out of reach of children.In case of overdose, get medical help or contact a Poison control Center right away.

Directions

- do not take more than 6 doses in any 24 hour period
- this adul strength product is not intended for use in children under 12 years of age
- measure only with dosing cup provided
- keep dosing cup with product
- TSP = teaspoon

age | dose
adults and children 12 years and over | 2 teaspoons (10mL) every 4 hours
children undre 12 years | do not use

Other information

- each teaspoon (5mL) contains:sodium 3 mg
- store at 15-30°C (59-86ºF). Do not refrigetate.

INACTIVE INGREDIENT

anhydrous citric acid, FD&C yellow #6, flavor, glycerin, honey, propylene glycol, purified water, sodium benzoate, sorbitol solution, sucralose, xanthan gum

Questions or comments?

1-800-560-5223 Monday to Friday 9am-4pm, Eastern Time